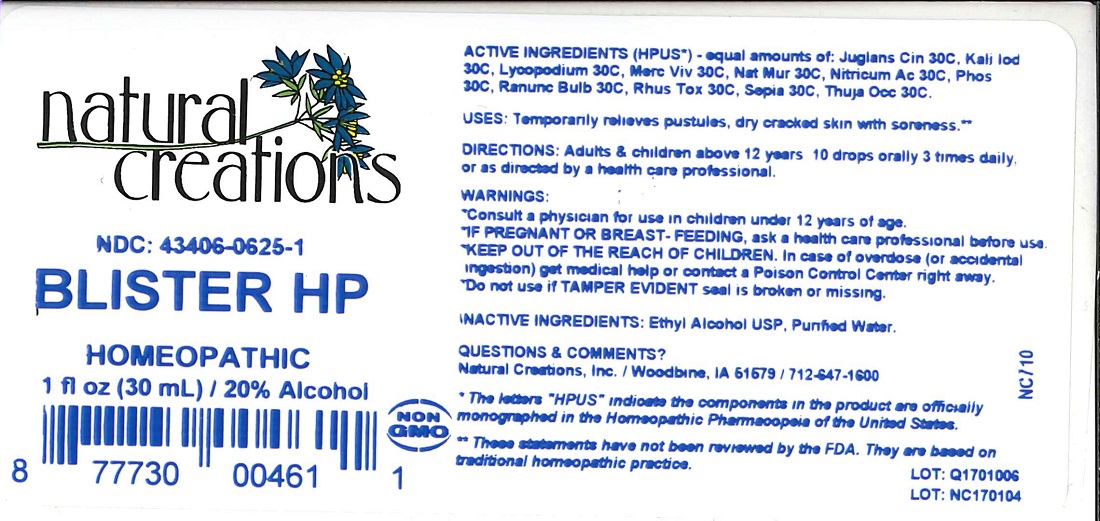 DRUG LABEL: BLISTER HP
NDC: 43406-0625 | Form: LIQUID
Manufacturer: Natural Creations, Inc.
Category: homeopathic | Type: HUMAN OTC DRUG LABEL
Date: 20251113

ACTIVE INGREDIENTS: JUGLANS CINEREA BRANCH BARK/ROOT BARK 30 [hp_C]/1 mL; POTASSIUM IODIDE 30 [hp_C]/1 mL; LYCOPODIUM CLAVATUM SPORE 30 [hp_C]/1 mL; MERCURY 30 [hp_C]/1 mL; SODIUM CHLORIDE 30 [hp_C]/1 mL; NITRIC ACID 30 [hp_C]/1 mL; PHOSPHORUS 30 [hp_C]/1 mL; RANUNCULUS BULBOSUS 30 [hp_C]/1 mL; TOXICODENDRON PUBESCENS LEAF 30 [hp_C]/1 mL; SEPIA OFFICINALIS JUICE 30 [hp_C]/1 mL; THUJA OCCIDENTALIS LEAFY TWIG 30 [hp_C]/1 mL
INACTIVE INGREDIENTS: ALCOHOL; water

BLISTER HP

ACTIVE INGREDIENT

ACTIVE INGREDIENTS (HPUS*) - equal amounts of: Juglans Cin 30C, Kali Iod 30C, Lycopodium 30C, Merc Viv 30C, Nat Mur 30C, Nitricum Ac 30C, Phos 30C, Ranun Bulb 30C, Rhus Tox 30C, Sepia 30C, Thuja Occ 30C.

PURPOSE

USES: Temporarily relieves pustules, dry cracked skin with soreness.**

INDICATIONS AND USAGE

USES: Temporarily relieves pustules, dry cracked skin with soreness.**

DOSAGE AND ADMINISTRATION

DIRECTIONS: Adults & children above 12 years: 10 drops orally 3 times daily, or as directed by a health care professional.

WARNINGS:

* Consult a physician for use in children under 12 years of age.

* IF PREGNANT OR BREAST-FEEDING, ask a health care professional before use.

* KEEP OUT OF THE REACH OF CHILDREN. In case of overdose (or accidental ingestion) get medical help or contact a Poison Control Center right away

* Do not use if TAMPER EVIDENT seal is broken or missing.

KEEP OUT OF REACH OF CHILDREN

KEEP OUT OF THE REACH OF CHILDREN. In case of overdose (or accidental ingestion) get medical help or contact a Poison Control Center right away.

INACTIVE INGREDIENTS: Ethyl Alcohol USP, Purified Water.

QUESTIONS & COMMENTS?

Natural Creations, Inc. / Woodbine, IA 51579 / 712-647-1600

REFERENCES

* The letters "HPUS" indicate the components in the product are officially monographed in the Homeopathic Pharmacopeia of the United States.

** These products have not been reviewed by the FDA. They are based on traditional homeopathic practice.

LOT:

PACKAGE LABEL

NDC: 43406-0625-1

BLISTER HP

HOMEOPATHIC

1 fl oz (30 mL) / 20% Alcohol

UPC: 877730004611